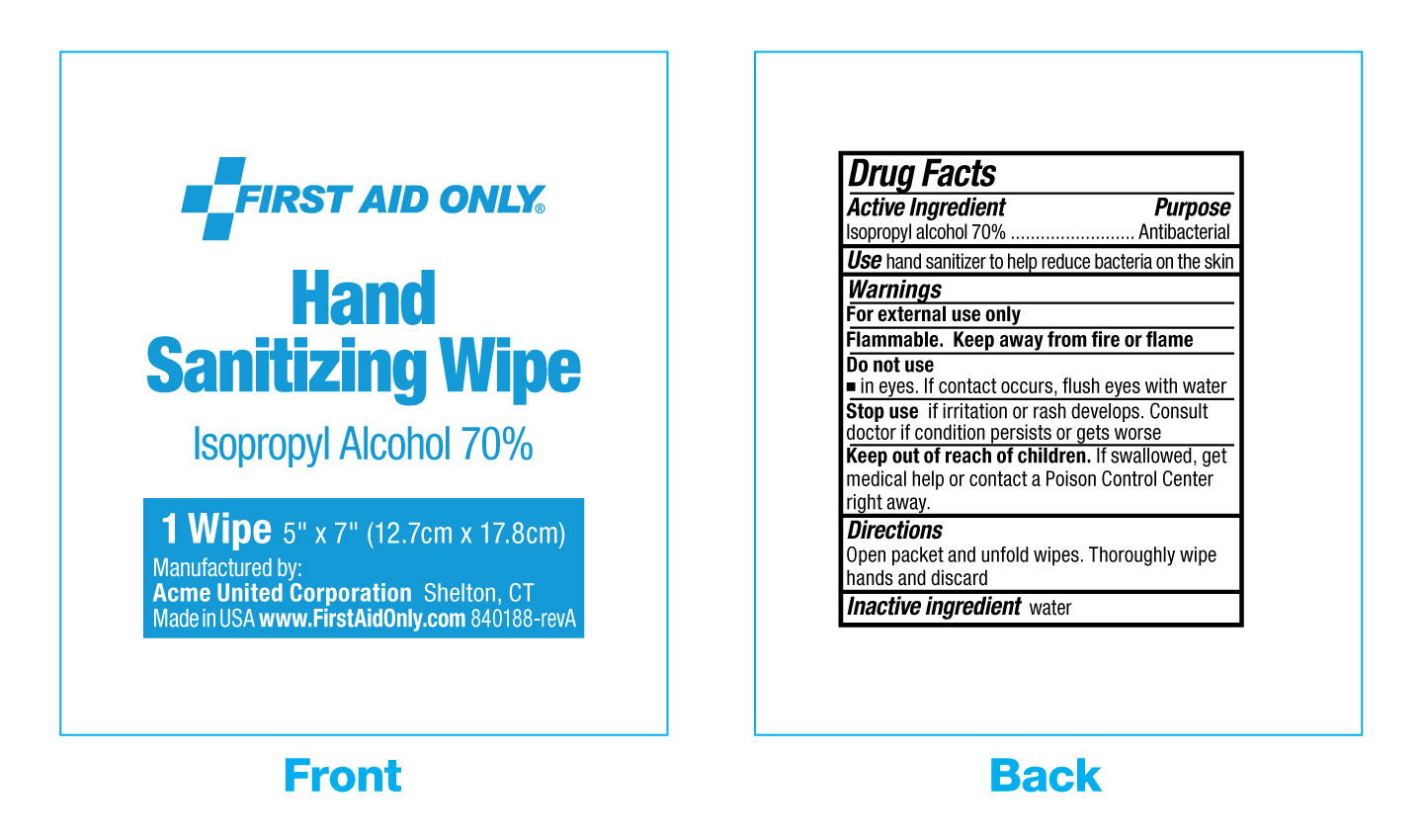 DRUG LABEL: First Aid Only Hand Sanitizing Wipe
NDC: 0924-0301 | Form: SWAB
Manufacturer: Acme United Corporation
Category: otc | Type: HUMAN OTC DRUG LABEL
Date: 20241126

ACTIVE INGREDIENTS: ISOPROPYL ALCOHOL 70 mL/100 mL
INACTIVE INGREDIENTS: WATER

First Aid Only Hand Sanitizing Wipe

Active Ingredient

Isopropyl Alcohol 70%

Purpose

Antibacterial

USE

hand sanitizer to hlp reduce bacteria on the skin

Warnings

For external use only

Flammable. Keep away from fire or flame

Do not use

•in eyes. If contact occurs, flush eyes with water

Stop use

if irritation or rash develops. Consult a doctor if condirtion persists or gets worse

Keep out of reach of children.

If swallowed, get medical help or contact a Poison Control Center right away.

Directions

Open packet and unfold wipes. Thoroughly wipe hands and discard

Inactive Ingredient

water

packet label